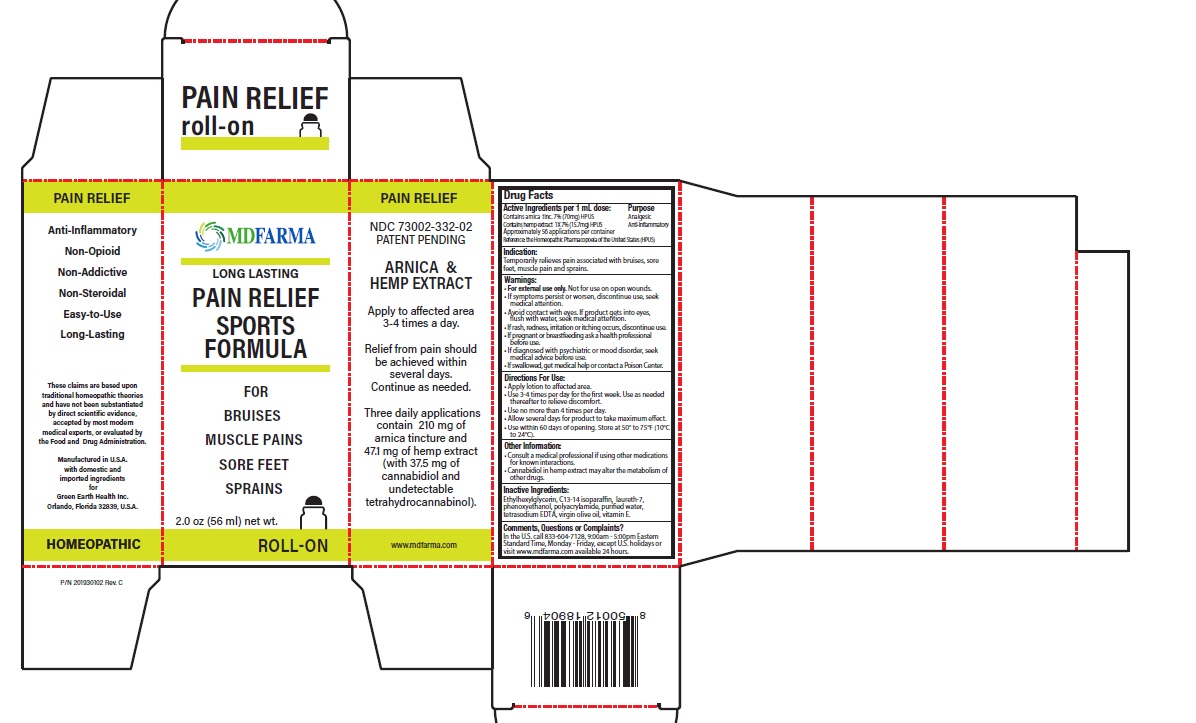 DRUG LABEL: PAIN RELIEF ARNICA AND HEMP
NDC: 73002-332 | Form: LOTION
Manufacturer: Green Earth Health Inc.
Category: homeopathic | Type: HUMAN OTC DRUG LABEL
Date: 20250722

ACTIVE INGREDIENTS: ARNICA MONTANA FLOWER 70 mg/1 mL; CANNABIS SATIVA SUBSP. SATIVA FLOWERING TOP 15.7 mg/1 mL
INACTIVE INGREDIENTS: C13-14 ISOPARAFFIN; LAURETH-7; POLYACRYLAMIDE (CROSSLINKED; 0.01-0.2 MOLE PERCENT BISACRYLAMIDE); WATER; OLIVE OIL; .ALPHA.-TOCOPHEROL; PHENOXYETHANOL; ETHYLHEXYLGLYCERIN; EDETATE SODIUM

Drug Facts

Active Ingredients Purpose

Arnica (A. montana) Tinc. 7% (70mg)HPUS Analgesic
Hemp extract (Cannabis sativa) 1X 7% (15.7mg) HPUS Anti-inflammatory

Approximately 56 applications per container

Reference: the Homeopathic Pharmacopoeia of the United States (HPUS)

Indication:

Temporarily relieves pain associated with bruises, sore feet, muscle pain and strains

Warnings:

• For external use only.Not for use on open wounds.
• If symptoms persist or worsen, discontinue use, seek medical attention.
• Avoid contact with eyes. If product gets into eyes, flush with water, seek medical attention.
• If rash, redness, irritation or itching occurs, discontinue use.
• If pregnant or breastfeeding ask a health professional before use.
• If diagnosed with psychiatric or mood disorder, seek medical advice before use.
• If swallowed, get medical help or contact a Poison Center.
• Keep out of reach of children.

Directions For Use:

- Liberally apply gel to affected area and rub into joints.
- Use 3-4 times per day for the first week. Use as needed thereafter to relieve discomfort.
- Use no more than 4 times per day.
- Allow several days for product to take maximum effect.
- Use within 60 days from opening. Store at 50° to 75°F (10°C to 24°C)

Other Information:

• Consult a medical professional if using other medications for known interactions.
• Cannabidiol in hemp extract may alter the metabolism of other drugs.

Inactive Ingredients:

Ethylglycerin, C13-14 isoparaffin, laureth-7, phenoxyethanol, polyacrylamide, purified water, tetrasodium EDTA, virgin olive oil, vitamin E